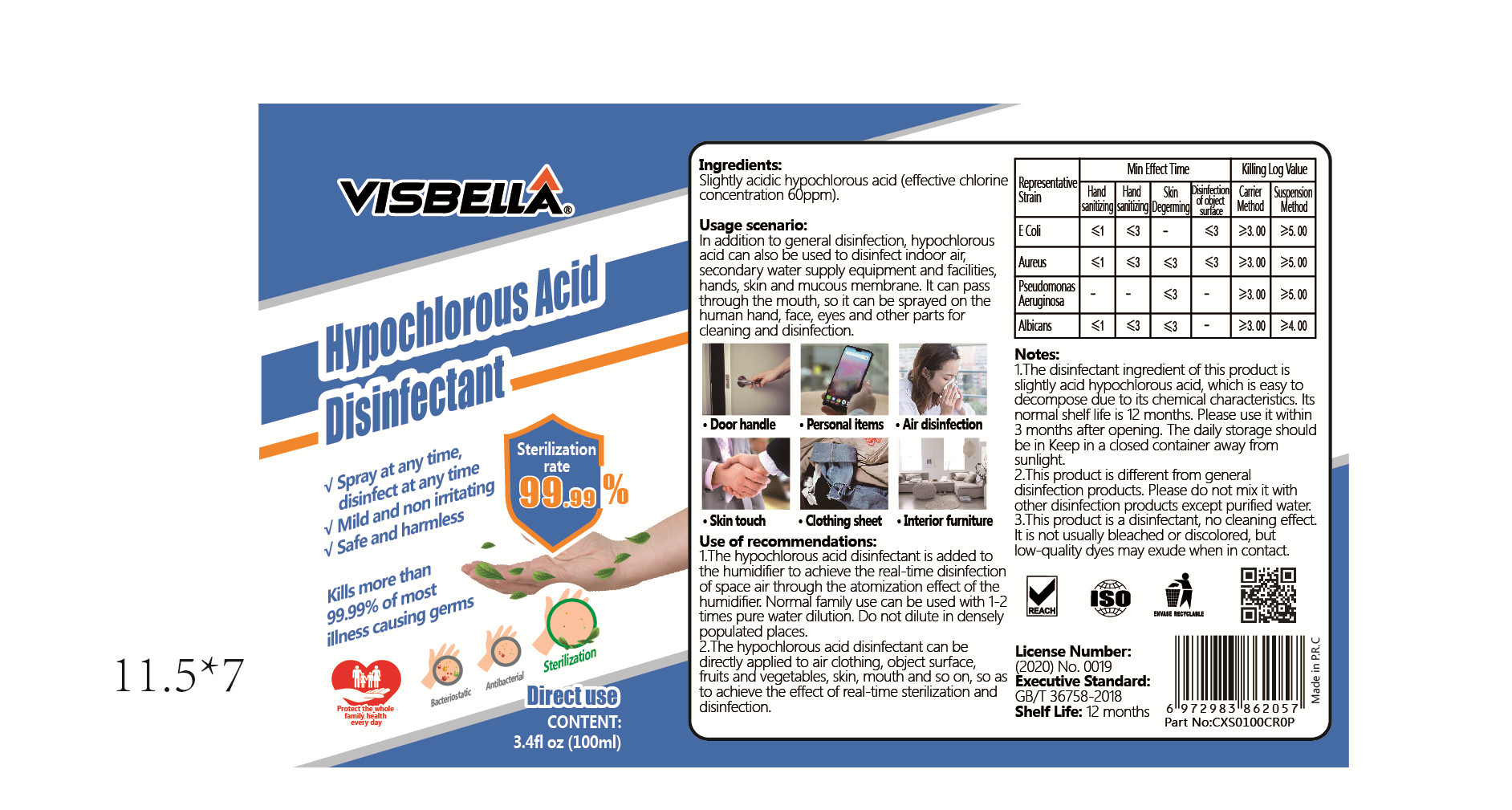 DRUG LABEL: VISBELLA Hypochlorous  acid disinfectant
NDC: 40760-013 | Form: LIQUID
Manufacturer: Huzhou Guoneng New Material Co., Ltd.
Category: otc | Type: HUMAN OTC DRUG LABEL
Date: 20200603

ACTIVE INGREDIENTS: HYPOCHLOROUS ACID 6 mg/100 mL
INACTIVE INGREDIENTS: WATER

DOSAGE AND ADMINISTRATION

The daily storage should be in Keep in a closed container away from sunlight.

INACTIVE INGREDIENT

WATER

INDICATIONS AND USAGE

1.The hypochlorous acid disinfectant is added to the humidifer to achieve the real-time disinfection of space air through the atomization effect of the humidifier. Normal family use can be used with 1-2 times pure water dilution. Do not dilute in densely populated places.
2.The hypochlorous acid disinfectant can be directly applied to air clothing, object surface,fruits and vegetables, skin, mouthi and so on, so as to achieve the effect of real-time sterilization and disinfection.

ACTIVE INGREDIENT

Hypochlorous acid

keep out of reach of children

PURPOSE

Disinfection
Sterilization

WARNINGS

1.The disinfectant ingredient of this product is slightly acid hypochlorous acid, which is easy to decompose due to its chemical characteristics. lts normal shelf life is 12 months. Please use it within 3 months after opening. The daily storage should be in Keep in a closed container away from sunlight.
2.This product is different from general disinfection products. Please do not mix it with other disinfection products except purifed water.
3.This product is a disinfectant, no cleaning effect.It is not usually bleached or discolored, but low-quality dyes may exude when in contact.